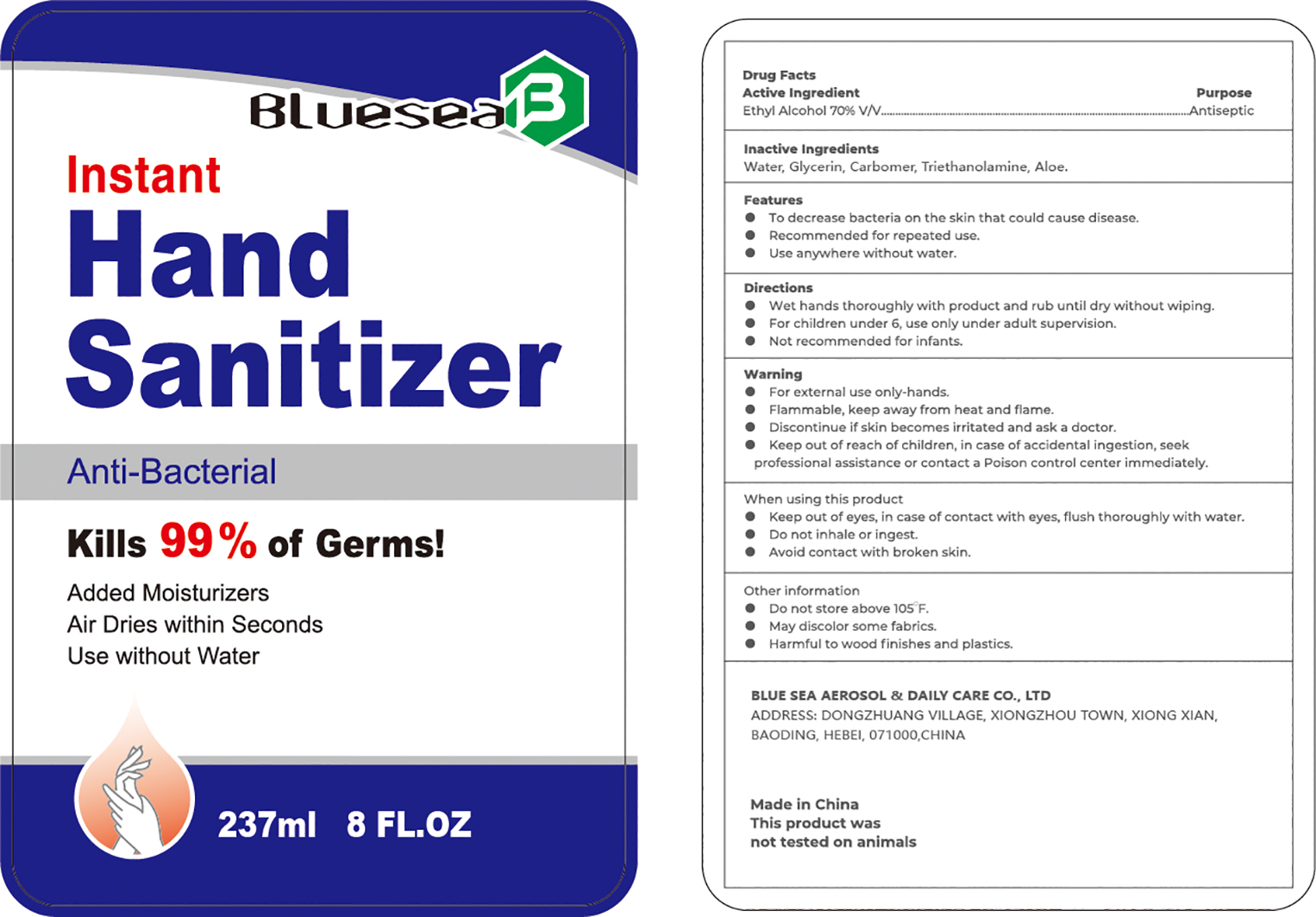 DRUG LABEL: BLUESEA INSTANT HAND SANITIZER
NDC: 72119-003 | Form: SOLUTION
Manufacturer: BLUE SEA AEROSOL & DAILY CARE CO., LTD
Category: otc | Type: HUMAN OTC DRUG LABEL
Date: 20241206

ACTIVE INGREDIENTS: ALCOHOL 70 mL/100 mL
INACTIVE INGREDIENTS: GLYCERIN; WATER; CARBOMER 934; TROLAMINE; ALOE

-003

Active Ingredient(s)

Ethyl Alcohol 75% v/v

Purpose

Antiseptic

Use

To decrease bacteria on the skin that could cause disease

Recommended for repeated use

Use anywhere without water

Warnings

For external use only -hands

Flammable. Keep away from heat and flame

When using this product keep out of eyes. In case of contact with eyes, flush thoroughly with water.

Avoid contact with broken skin

Do not inhale or ingest

STOP USE

Discontinue if skin becomes irritated and ask a doctor

Keep out of reach of children. In case of accidental ingest, seek professional assistance or contact a Poison Control Center right away.

Directions

- Wet hands thoroughly with product and rub until dry without wiping
- For children under 6, use only under adult supervision
- Not recommended for infants

Other information

Do not store above 105F

May discolor some fabrics

Harmful to wood finishes and plastics

Inactive ingredients

Water, glycerin, carbomer, triethanolamine, Aloe